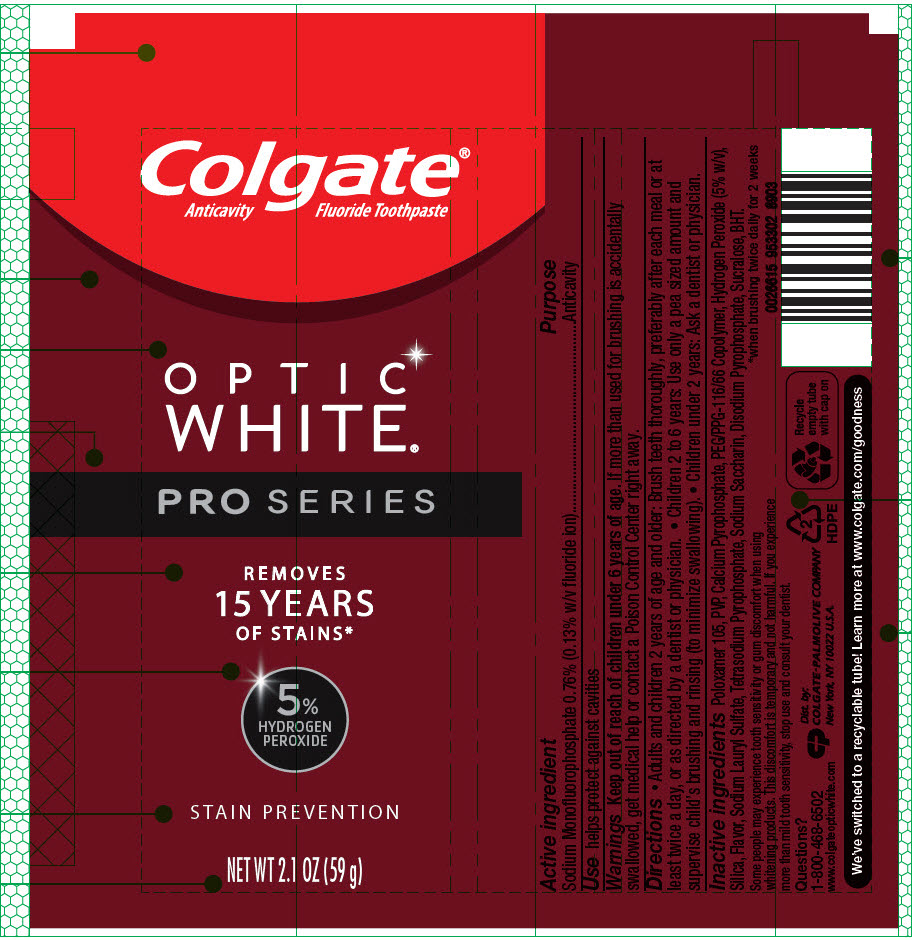 DRUG LABEL: Colgate Optic White Pro Series Stain Prevention
NDC: 35000-747 | Form: PASTE, DENTIFRICE
Manufacturer: Colgate-Palmolive Company
Category: otc | Type: HUMAN OTC DRUG LABEL
Date: 20191031

ACTIVE INGREDIENTS: SODIUM MONOFLUOROPHOSPHATE 1.1 mg/1 g
INACTIVE INGREDIENTS: POLOXAMER 105 450.3 mg/1 g; CROSPOVIDONE, UNSPECIFIED; CALCIUM PYROPHOSPHATE; PEG/PPG-116/66 COPOLYMER; HYDROGEN PEROXIDE; SILICON DIOXIDE; SODIUM LAURYL SULFATE; SODIUM PYROPHOSPHATE; SACCHARIN SODIUM; SODIUM ACID PYROPHOSPHATE; SUCRALOSE; BUTYLATED HYDROXYTOLUENE

Colgate® Optic White® Pro Series Stain Prevention

Active ingredients

Sodium Monofluorophosphate 0.76% (0.13% w/v fluoride ion)

Purpose

Anticavity

Use

helps protect against cavities

Warnings

Keep out of reach of children under 6 years of age. If more than used for brushing is accidentally swallowed, get medical help or contact a Poison Control Center right away.

Directions

- Adults and children 2 years of age and older: Brush teeth thoroughly, preferably after each meal or at least twice a day, or as directed by a dentist or physician.
- Children 2 to 6 years: Use only a pea sized amount and supervise child's brushing and rinsing (to minimize swallowing).
- Children under 2 years: Ask a dentist or physician.

Inactive ingredients

Poloxamer 105, PVP, Calcium Pyrophosphate, PEG/PPG-116/66 Copolymer, Hydrogen Peroxide (5% w/v), Silica, Flavor, Sodium Lauryl Sulfate, Tetrasodium Pyrophosphate, Sodium Saccharin, Disodium Pyrophosphate, Sucralose, BHT.

Questions?

1-800-468-6502
www.colgateopticwhite.com

Dist. by:
COLGATE-PALMOLIVE COMPANY
New York, NY 10022 U.S.A.

PRINCIPAL DISPLAY PANEL - 59 g Tube Label

Colgate®
Anticavity Fluoride Toothpaste

OPTIC
WHITE®

PRO SERIES

REMOVES
15 YEARS
OF STAINS*

5%
HYDROGEN
PEROXIDE

STAIN PREVENTION

NET WT 2.1 OZ (59 g)